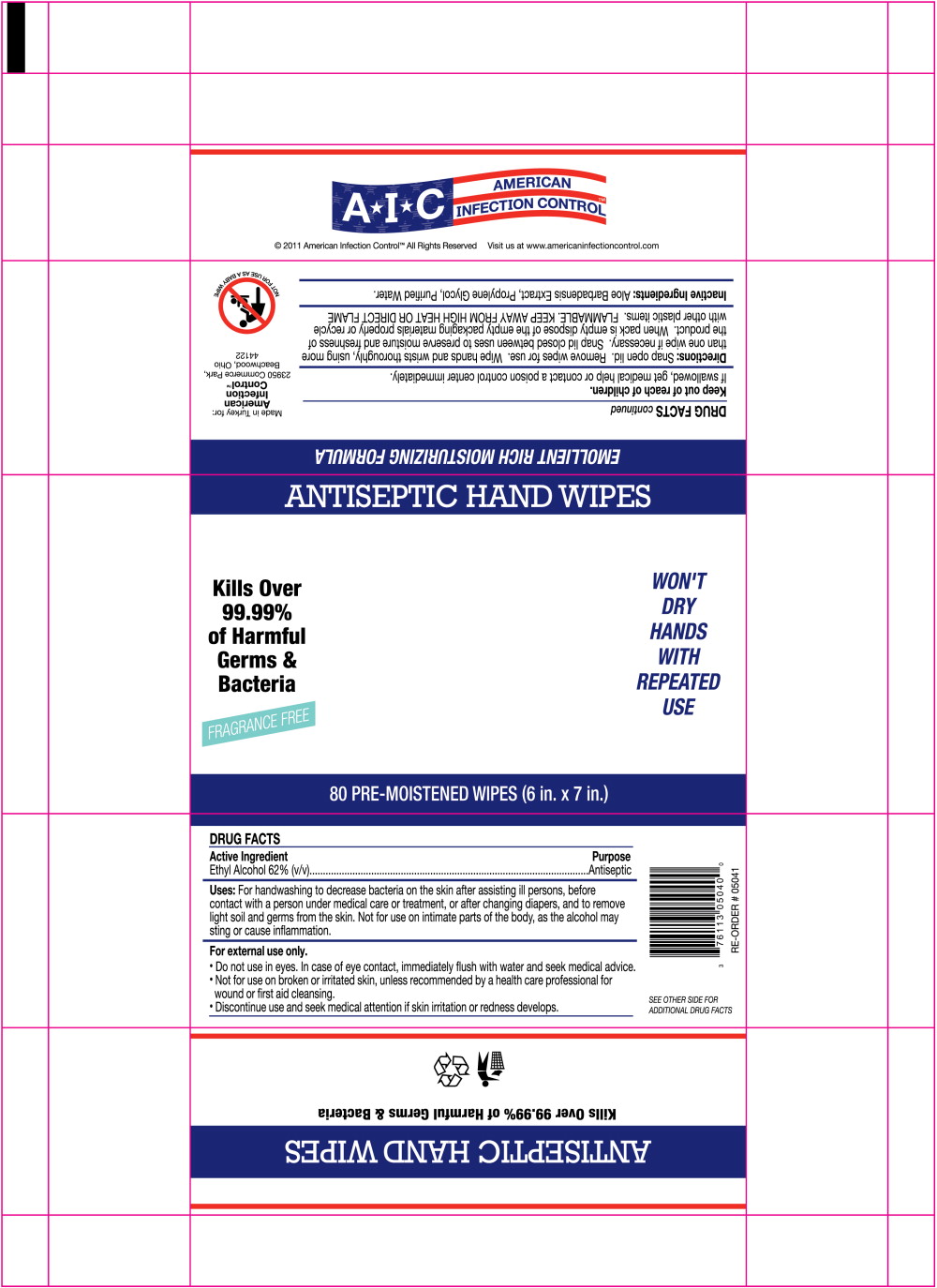 DRUG LABEL: American Infection Control Antiseptic Hand Wipes
NDC: 76113-012 | Form: CLOTH
Manufacturer: American Infection Control, Inc.
Category: otc | Type: HUMAN OTC DRUG LABEL
Date: 20120206

ACTIVE INGREDIENTS: Alcohol .62 mL/1 mL
INACTIVE INGREDIENTS: Aloe Vera Leaf; Propylene Glycol; Water

DRUG FACTS

Active Ingredient

Ethyl Alcohol 62% (v/v)

Purpose

Antiseptic

Uses:

For handwashing to decrease bacteria on the skin after assisting ill persons, before contact with a person under medical care or treatment, or after changing diapers, and to remove light soil and germs from the skin. Not for use on intimate parts of the body, as the alcohol may sting or cause inflammation.

WARNINGS

For external use only.

- Do not use in eyes. In case of eye contact, immediately flush with water and seek medical advice.
- Not for use on broken or irritated skin, unless recommended by a health care professional for wound or first aid cleansing.
- Discontinue use and seek medical attention if skin irritation or redness develops.

Keep out of reach of children.

If swallowed, get medical help or contact a poison control center immediately.

Directions:

Snap open lid. Remove wipes for use. Wipe hands and wrists thoroughly, using more than one wipe if necessary. Snap lid closed between uses to preserve moisture and freshness of the product. When pack is empty dispose of the empty packaging materials properly or recycle with other plastic items. FLAMMABLE. KEEP AWAY FROM HIGH HEAT OR DIRECT FLAME

Inactive Ingredients:

Aloe Barbadensis Extract, Propylene Glycol, Purified Water.

Principal Display Panel – Package Label

ANTISEPTIC HAND WIPES

Kills Over WON'T
99.99% DRY
of Harmful HANDS
Germs & WITH
Bacteria REPEATED
FRAGRANCE FREE USE

80 PRE-MOISTENED WIPES (6 in. x 7 in.)